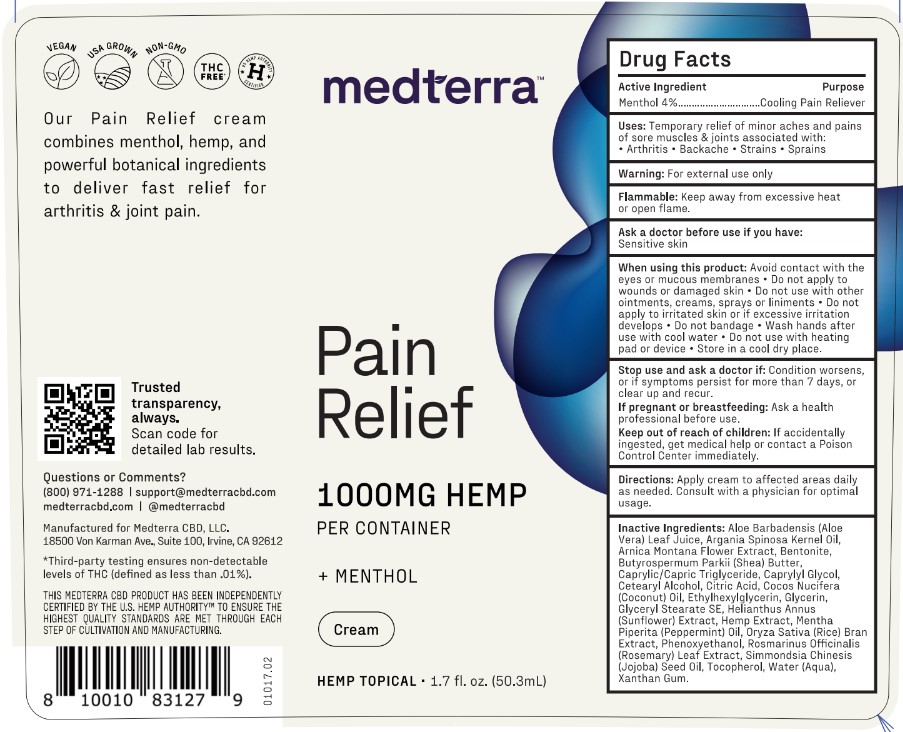 DRUG LABEL: Medterra Pain Relief 1000mg Hemp Menthol Cream
NDC: 83696-603 | Form: CREAM
Manufacturer: Respect Manufacturing Corporation
Category: otc | Type: HUMAN OTC DRUG LABEL
Date: 20250623

ACTIVE INGREDIENTS: MENTHOL, UNSPECIFIED FORM 2.012 g/50.3 g
INACTIVE INGREDIENTS: TOCOPHEROL; ALOE VERA LEAF; PEPPERMINT OIL; WATER; GLYCERYL STEARATE SE; SUNFLOWER SEED; RICE BRAN; XANTHAN GUM; GLYCERIN; JOJOBA OIL; SHEA BUTTER; CITRIC ACID MONOHYDRATE; CAPRYLYL GLYCOL; ARGAN OIL; PHENOXYETHANOL; ROSEMARY; CETOSTEARYL ALCOHOL; COCONUT OIL; ARNICA MONTANA FLOWER; ETHYLHEXYLGLYCERIN; HEMP; MEDIUM-CHAIN TRIGLYCERIDES; BENTONITE

Medterra Pain Relief 1000mg Hemp Menthol Cream

Active Ingredient

Menthol 4%

Purpose

Cooling Pain Reliever

Uses:

Temporary relief of minor aches and pains of sore muscles & joints associated with: Arthritis · Backache · Strains · Sprains

Warnings:

For external use only.

Flammable:

Keep away from excessive heat or open flame.

Ask a doctor before use if you have:

Sensitive skin

When using this product:

Avoid contact with the eyes or mucous membranes • Do not apply to wounds or damaged skin • Do not use with other ointments, creams, sprays or liniments • Do not apply to irritated skin or if excessive irritation develops • Do not bandage • Wash hands after use with cool water • Do not use with heating pad or device • Store in a cool dry place.

Stop use and ask a doctor if:

Conditions worsens, or if symptoms persist for more than 7 days, or clear up and recur.

If pregnant or breastfeeding:

Ask a health professional before use.

Keep out of reach of children:

If accidentally ingested, get medical help or contact a Poison Control Center immediately.

Directions:

Apply cream to affected areas daily as needed. Consult with a physician for optimal usage.

Inactive Ingredients:

Aloe Barbadensis (Aloe Vera) Leaf Juice, Argania Spinosa Kernel Oil, Arnica Montana Flower Extract, Bentonite, Butyrospermum Parkii (shea) Butter, Caprylic/Capric Triglyceride, Caprylyl Glycol, Cetearyl Alcohol, Citric Acid, Cocos Nucifera (Coconut) Oil, Ethylhexylglycerin, Glycerin, Glyceryl Stearate SE, Helianthus Annus (Sunflower) Extract, Hemp Extract, Mentha Piperita (Peppermint) Oil, Oryza Sativa (Rice) Bran Extract, Phenoxyethanol, Rosmarinus Officinalis (Rosemary) Leaf Extract, Simmondsia Chinesis (Jojoba) Seed Oil, Tocopherol, Water (Aqua), Xanthan Gum.

Questions or Comments?

(800) 971-1288 | support@medterracbd.com

medterracbd.com | @medterracbd.com

Manufactured for Medterra CBD, LLC.

18500 Von Karman Ave., Suite 100, Irvine, CA 92612

*Third-party testing ensures non-detectable levels of THC (defined as less than .01%)

THIS MEDTERRA CBD PRODUCT HAS BEEN INDEPENDENTLY CERTIFIED BY THE U.S. HEMP AUTHORITY™ TO ENSURE THE HIGHEST QUALITY STANDARDS ARE MET THROUGH EACH STEP OF CULTIVATION AND MANUFACTURING.

PACKAGE LABEL

medterra

Pain

Relief

1000MG Hemp

per container

+ MENTHOL

Cream

Hemp Topical · 1.7 fl. oz. (50.3mL)

Our Pain Relief cream combines menthol, hemp, and powerful botanical ingredients to deliver fast relief for arthritis & joint pain.

Trusted transparency, always.

Scan code for detailed lab results.